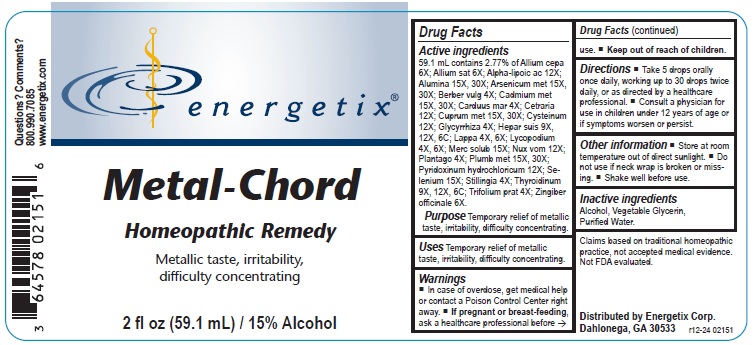 DRUG LABEL: Metal-Chord
NDC: 64578-0068 | Form: LIQUID
Manufacturer: Energetix Corporation
Category: homeopathic | Type: HUMAN OTC DRUG LABEL
Date: 20250715

ACTIVE INGREDIENTS: ONION 6 [hp_X]/1 mL; GARLIC 6 [hp_X]/1 mL; .ALPHA.-LIPOIC ACID 12 [hp_X]/1 mL; ALUMINUM OXIDE 15 [hp_X]/1 mL; ARSENIC 15 [hp_X]/1 mL; BERBERIS VULGARIS ROOT BARK 4 [hp_X]/1 mL; CADMIUM 15 [hp_X]/1 mL; MILK THISTLE 4 [hp_X]/1 mL; CETRARIA ISLANDICA SUBSP. ISLANDICA 12 [hp_X]/1 mL; COPPER 15 [hp_X]/1 mL; CYSTEINE 12 [hp_X]/1 mL; GLYCYRRHIZA GLABRA 4 [hp_X]/1 mL; PORK LIVER 9 [hp_X]/1 mL; ARCTIUM LAPPA ROOT 4 [hp_X]/1 mL; LYCOPODIUM CLAVATUM SPORE 4 [hp_X]/1 mL; MERCURIUS SOLUBILIS 15 [hp_X]/1 mL; STRYCHNOS NUX-VOMICA SEED 12 [hp_X]/1 mL; PLANTAGO MAJOR 4 [hp_X]/1 mL; LEAD 15 [hp_X]/1 mL; PYRIDOXINE HYDROCHLORIDE 12 [hp_X]/1 mL; SELENIUM 15 [hp_X]/1 mL; STILLINGIA SYLVATICA ROOT 4 [hp_X]/1 mL; THYROID, BOVINE 9 [hp_X]/1 mL; TRIFOLIUM PRATENSE FLOWER 4 [hp_X]/1 mL; GINGER 6 [hp_X]/1 mL
INACTIVE INGREDIENTS: WATER; GLYCERIN; ALCOHOL

Metal-Chord

ACTIVE INGREDIENT

Active ingredients 59.1 mL contains 2.77% of: Allium cepa 6X; Allium sat 6X; Alpha-lipoic ac 12X; Alumina 15X, 30X; Arsenicum met 15X, 30X; Berber vulg 4X; Cadmium met 15X, 30X; Carduus mar 4X; Cetraria 12X; Cuprum met 15X, 30X; Cysteinum 12X; Glycyrrhiza 4X; Hepar
suis 9X, 12X, 6C; Lappa 4X, 6X; Lycopodium 4X, 6X; Merc solub 15X; Nux vom 12X; Plantago 4X; Plumb met 15X, 30X; Pyridoxinum hydrochloricum 12X; Selenium 15X; Stillingia 4X; Thyroidinum 9X, 12X, 6C; Trifolium prat 4X; Zingiber officinale 6X

Claims based on traditional homeopathic practice, not accepted medical evidence. Not FDA evaluated.

INDICATIONS AND USAGE

Uses Temporary relief of metallic taste, irritability, difficulty concentrating.

Warnings

- In case of overdose, get medical help or call a Poison Control Center right away.
- If pregnant or breast-feeding,ask a health professional before use.

- Keep out of reach of children.

Directions

- Take 5 drops orally once daily, working up to 30 drops twice daily, or as directed by a healthcare professional.
- Consult a physician for use in children under 12 years of age or if symptoms worsen or persist.

Other information

- Store at room temperature out of direct sunlight.
- Do not use if neck wrap is broken or missing.
- Shake well before use.

Inactive ingredients Alcohol, Vegetable Glycerin, Purified Water

QUESTIONS

Distributed by
Energetix Corp
Dahlonega, GA 30533
Questions? Comments? 800.990.7085

www.energetix.com

PACKAGE LABEL

energetix
Metal-Chord
Homeopathic Remedy
Metallic taste, irritability,
difficulty concentrating
2 fl oz (59.1 mL) / 15% Alcohol

PURPOSE

Purpose Temporary relief of metallic taste, irritability, difficulty concentrating.